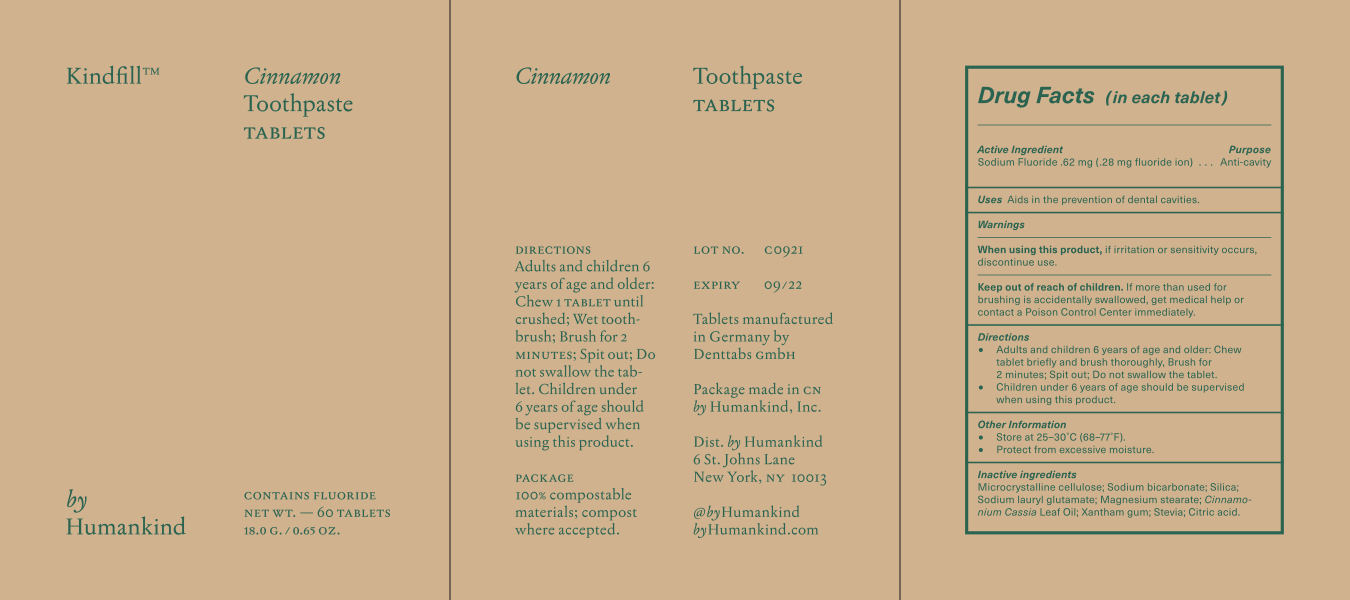 DRUG LABEL: Kindfill
NDC: 80487-322 | Form: TABLET, CHEWABLE
Manufacturer: By Humankind Inc
Category: otc | Type: HUMAN OTC DRUG LABEL
Date: 20241227

ACTIVE INGREDIENTS: SODIUM FLUORIDE 0.62 mg/1 1
INACTIVE INGREDIENTS: STEVIA LEAF; CITRIC ACID MONOHYDRATE; SODIUM BICARBONATE; SILICON DIOXIDE; MICROCRYSTALLINE CELLULOSE; MINT; XANTHAN GUM; SODIUM LAUROYL GLUTAMATE; MAGNESIUM STEARATE

BYHUMANKIND-Identipak: Cinnamon

Active Ingredient(s)

Sodium Fluoride .62mg (28 mg flouride ion)

Purpose

Anti-cavity

Use

aids in the prevention of dental cavities

Warnings

- When using this product, if irritation or sensitivity occurs discontinue use.
- Keep out of the reach of children. If more than used for brushing is accidentally swallowed, get medical help or contact a Poison Control Center immediately.

When using this product, if irritation or sensitivity occurs discontinue use.

KEEP OUT OF REACH OF CHILDREN

If more than used for brushing is accidentally swallowed, get medical help or contact a Poison Control Center immediately.

Directions

- Adults and children 6 years and older; chew one tablet until crushed, wet toothbrush, brush for 2 minutes. Spit out.
- Do not swallow the tablet.
- Children under 6 years of age should be supervised when using this product.

Other information

Store at 25-30°C (68-77°F). Protect from excessive moisture.

Inactive ingredients

Microcrystalline Cellulose, Sodium bicarbonate (Baking Soda), Silica, Sodium Lauryl Glutamate, Magnesium Stearate, Xanthan Gum, Stevia (Stevioside), Citric Acid

Package Label - Principal Display Panel

60 in Each Box NDC: 80487-322-11